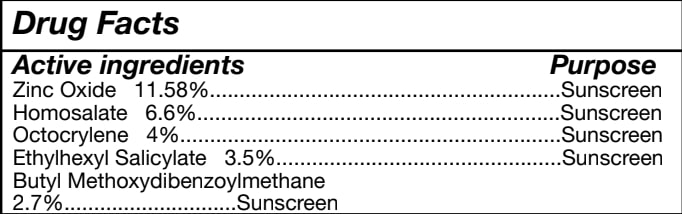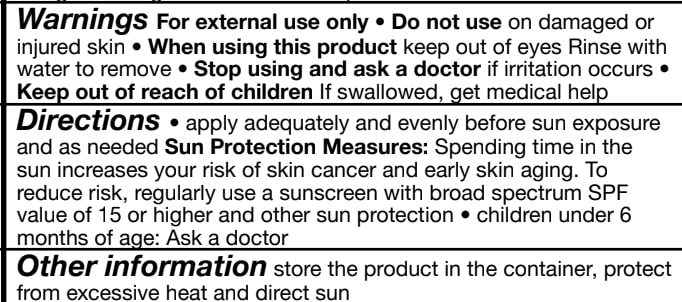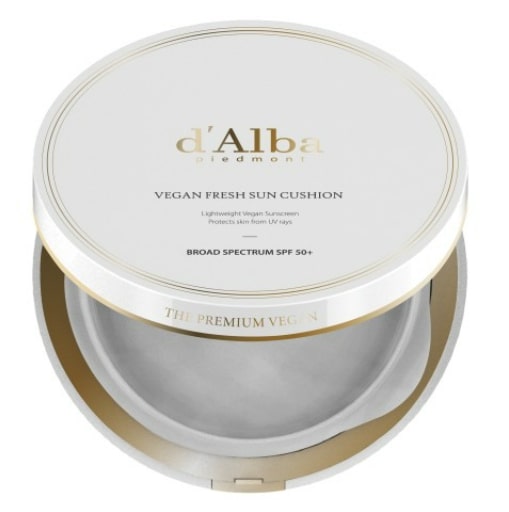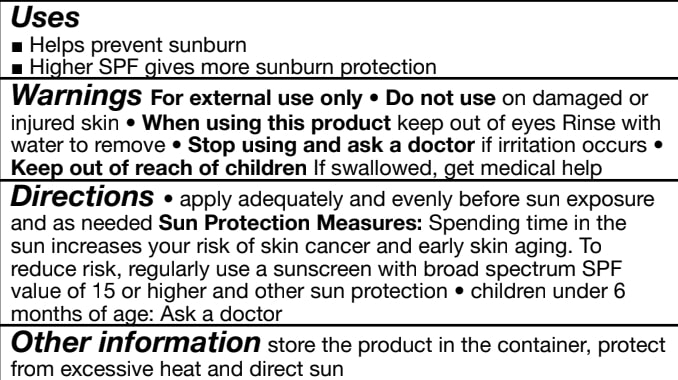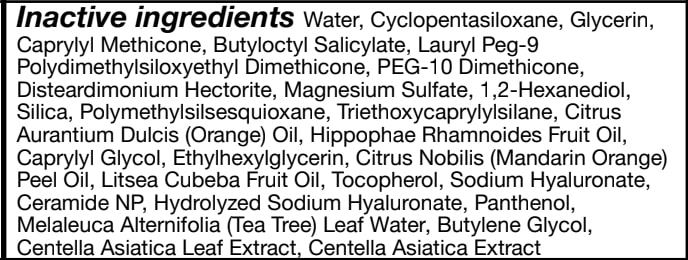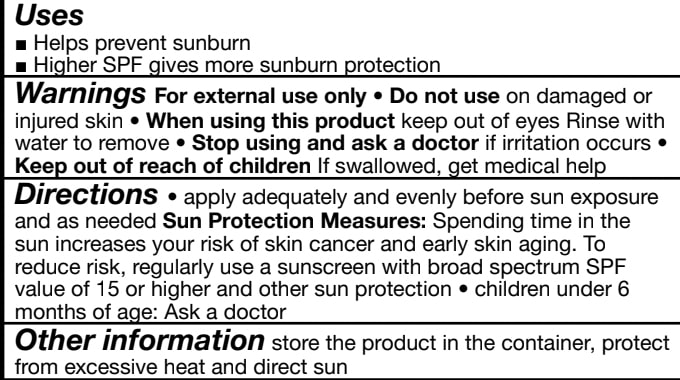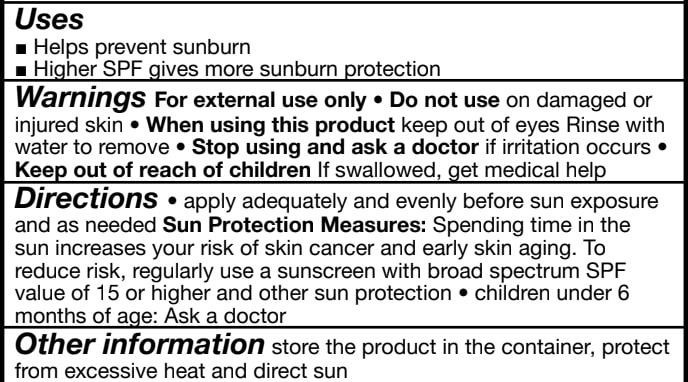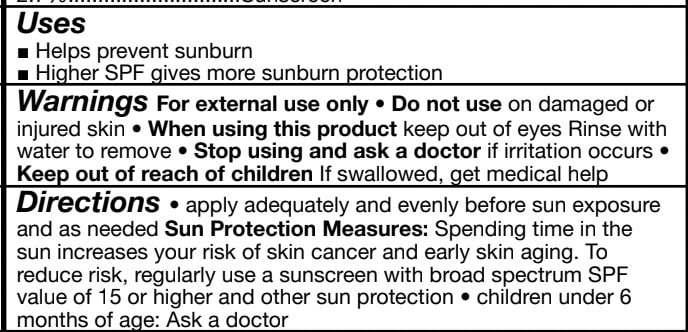 DRUG LABEL: dAlba Vegan Fresh Sun Cushion
NDC: 84662-060 | Form: SPONGE
Manufacturer: ADMTMAX LLC
Category: otc | Type: HUMAN OTC DRUG LABEL
Date: 20250608

ACTIVE INGREDIENTS: ZINC OXIDE 11.58 mg/25 g
INACTIVE INGREDIENTS: GLYCERIN

d'Alba Vegan Fresh Sun Cushion